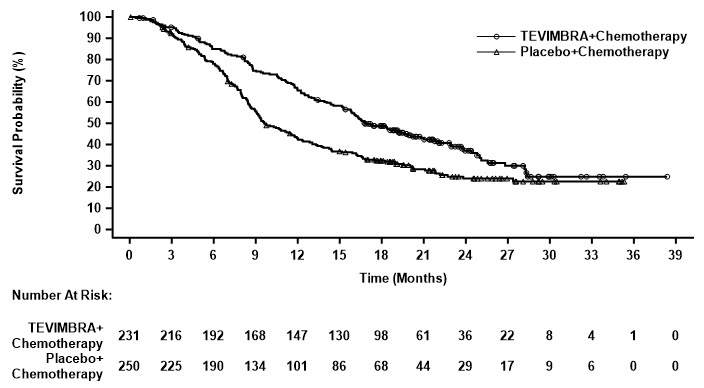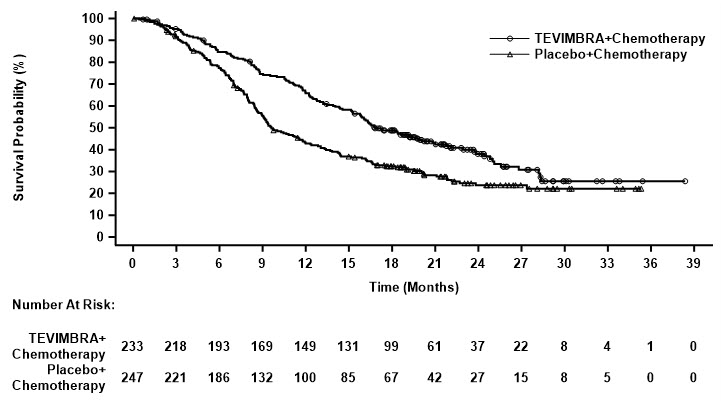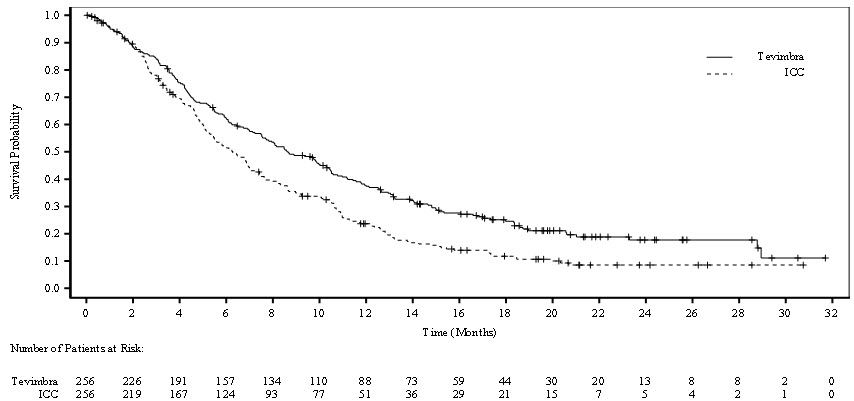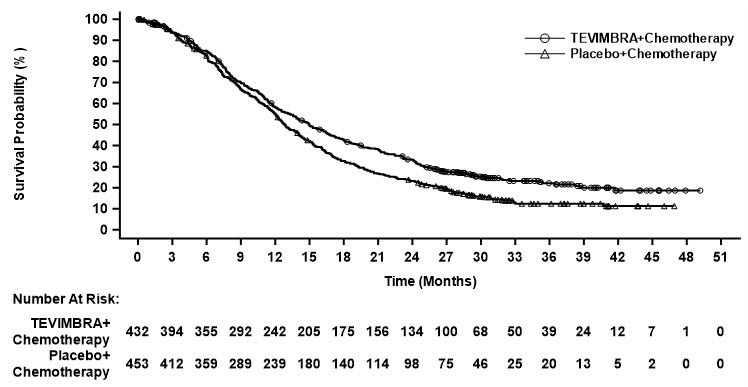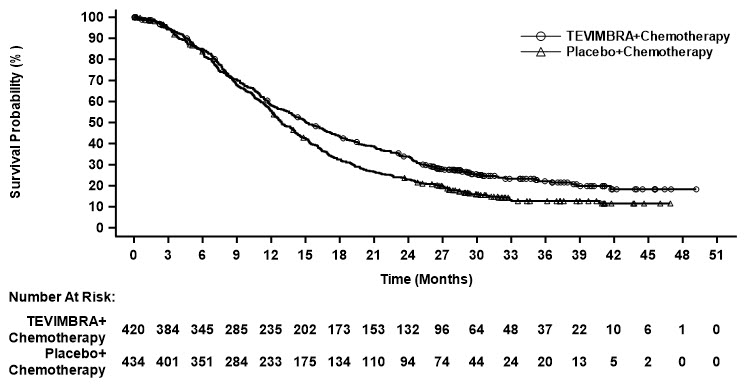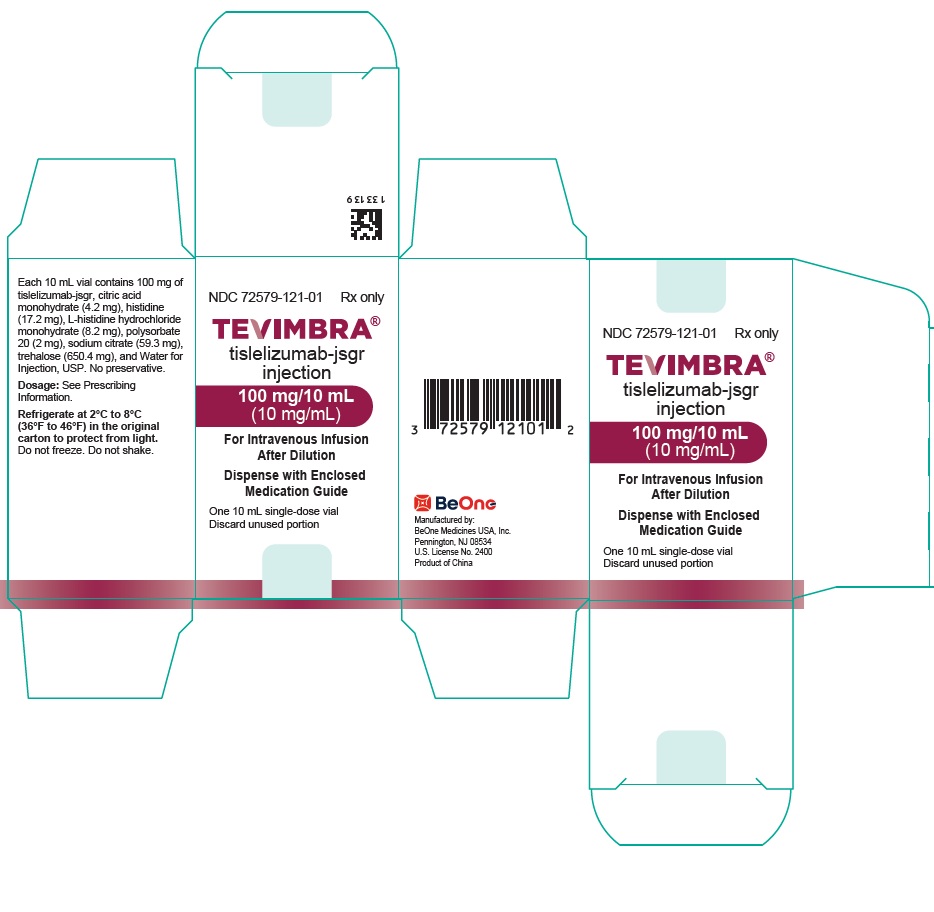 DRUG LABEL: TEVIMBRA
NDC: 72579-121 | Form: INJECTION, SOLUTION, CONCENTRATE
Manufacturer: BeOne Medicines USA, Inc.
Category: prescription | Type: HUMAN PRESCRIPTION DRUG LABEL
Date: 20260204

ACTIVE INGREDIENTS: TISLELIZUMAB 10 mg/1 mL
INACTIVE INGREDIENTS: CITRIC ACID MONOHYDRATE 0.42 mg/1 mL; HISTIDINE 2.54 mg/1 mL; POLYSORBATE 20 0.2 mg/1 mL; SODIUM CITRATE, UNSPECIFIED FORM 5.93 mg/1 mL; TREHALOSE 65.04 mg/1 mL; WATER

HIGHLIGHTS OF PRESCRIBING INFORMATION

These highlights do not include all the information needed to use TEVIMBRA safely and effectively. See full prescribing information for TEVIMBRA.
TEVIMBRA® (tislelizumab-jsgr) injection, for intravenous use
Initial U.S. Approval: 2024

RECENT MAJOR CHANGES

Indications and Usage (1.1, 1.2) | 3/2025
Dosage and Administration (2.1) | 3/2025
Dosage and Administration (2.2) | 12/2025
Dosage and Administration (2.4) | 11/2025

1 INDICATIONS AND USAGE

TEVIMBRA is a programmed death receptor-1 (PD-1)-blocking antibody indicated for:

Esophageal Cancer

- in combination with platinum-containing chemotherapy for the first-line treatment of adults with unresectable or metastatic esophageal squamous cell carcinoma (ESCC) whose tumors express PD-L1 (≥1). (1.1)
- as a single agent in adults with unresectable or metastatic esophageal squamous cell carcinoma (ESCC) after prior systemic chemotherapy that did not include a PD-(L)1 inhibitor. (1.1)

Gastric Cancer

- in combination with platinum and fluoropyrimidine-based chemotherapy in adults for the first line treatment of unresectable or metastatic HER2-negative gastric or gastroesophageal junction adenocarcinoma whose tumors express PD-L1 (≥1). (1.2)

2 DOSAGE AND ADMINISTRATION

Recommended Dosage:

Esophageal Cancer

- 150 mg every 2 weeks or 200 mg every 3 weeks or 300 mg every 4 weeks or 400 mg every 6 weeks in combination with platinum-containing chemotherapy for first-line treatment of unresectable or metastatic ESCC. (2.2)
- 150 mg every 2 weeks or 200 mg every 3 weeks or 300 mg every 4 weeks or 400 mg every 6 weeks as a single agent for treatment of unresectable or metastatic ESCC. (2.2)

Gastric Cancer

- 150 mg every 2 weeks or 200 mg every 3 weeks or 300 mg every 4 weeks or 400 mg every 6 weeks in combination with platinum and fluoropyrimidine-based chemotherapy. (2.2)

3 DOSAGE FORMS AND STRENGTHS

Injection: 100 mg/10 mL (10 mg/mL) solution in a single-dose vial. (3)

4 CONTRAINDICATIONS

None. (4)

5 WARNINGS AND PRECAUTIONS

- Immune-Mediated Adverse Reactions: (5.1)
  - Immune-mediated adverse reactions, which may be severe or fatal, can occur in any organ system or tissue, including the following: immune-mediated pneumonitis, immune-mediated colitis, immune-mediated hepatitis, immune-mediated endocrinopathies, immune-mediated nephritis with renal dysfunction, immune-mediated dermatologic adverse reactions, and solid organ transplant rejection.
  - Monitor for early identification and management. Evaluate liver enzymes, creatinine, and thyroid function at baseline and periodically during treatment.
  - Withhold or permanently discontinue TEVIMBRA based on the severity of reaction.
- Infusion-Related Reactions: Slow the rate of infusion, interrupt, or permanently discontinue based on severity of infusion reaction. (5.2)
- Complications of Allogeneic Hematopoietic Stem Cell Transplantation (HSCT): Fatal and other serious complications can occur in patients who receive allogeneic HSCT before or after being treated with a PD-1/PD-L1 blocking antibody. (5.3)
- Embryo-Fetal Toxicity: Can cause fetal harm. Advise females of reproductive potential of the potential risk to a fetus and to use effective contraception. (5.4, 8.1, 8.3)

6 ADVERSE REACTIONS

Most common adverse reactions (≥20%), including laboratory abnormalities, were:

- TEVIMBRA in combination with platinum-containing chemotherapy: decreased neutrophil count, decreased sodium, increased glucose, anemia, fatigue, decreased appetite, increased AST, decreased potassium, increased serum creatinine, decreased calcium, increased ALT, diarrhea, stomatitis, and vomiting. (6.1)
- TEVIMBRA as a single agent: increased glucose, decreased hemoglobin, decreased lymphocytes, decreased sodium, decreased albumin, increased alkaline phosphatase, anemia, fatigue, increased AST, musculoskeletal pain, decreased weight, increased ALT, and cough. (6.1)
- TEVIMBRA in combination with platinum and fluoropyrimidine-based chemotherapy: nausea, fatigue, decreased appetite, anemia, peripheral sensory neuropathy, vomiting, decreased platelet count, decreased neutrophil count, increased aspartate aminotransferase, diarrhea, abdominal pain, increased alanine aminotransferase, decreased white blood cell count, decreased weight, and pyrexia. (6.1)

To report SUSPECTED ADVERSE REACTIONS, contact BeOne Medicines at 1-877-828-5596 or FDA at 1-800-FDA-1088 or www.fda.gov/medwatch.

8 USE IN SPECIFIC POPULATIONS

Lactation: Advise not to breastfeed. (8.2)

FULL PRESCRIBING INFORMATION

1 INDICATIONS AND USAGE

1.1 Esophageal Cancer

- First-Line Treatment of Esophageal Squamous Cell Carcinoma

TEVIMBRA, in combination with platinum-containing chemotherapy, is indicated for the first-line treatment of adults with unresectable or metastatic esophageal squamous cell carcinoma (ESCC) whose tumors express PD-L1 (≥1).

- Previously Treated Esophageal Squamous Cell Carcinoma

TEVIMBRA, as a single agent, is indicated for the treatment of adults with unresectable or metastatic esophageal squamous cell carcinoma (ESCC) after prior systemic chemotherapy that did not include a PD-(L)1 inhibitor.

1.2 Gastric Cancer

TEVIMBRA, in combination with platinum and fluoropyrimidine-based chemotherapy, is indicated for the first-line treatment of adults with unresectable or metastatic HER2-negative gastric or gastroesophageal junction adenocarcinoma (G/GEJ) whose tumors express PD-L1 (≥1).

2 DOSAGE AND ADMINISTRATION

2.1 Patient Selection

Select patients for the first-line treatment of unresectable or metastatic esophageal squamous cell carcinoma based on the presence of PD-L1 in tumor specimens [see Clinical Studies (14.1)]. An FDA-approved companion diagnostic for the detection of PD-L1 in patients with unresectable or metastatic esophageal squamous cell carcinoma is not available.

Select patients for the first-line treatment of unresectable or metastatic HER2-negative gastric or gastroesophageal junction adenocarcinoma (G/GEJ) based on the presence of PD-L1 in tumor specimens [see Clinical Studies (14.2)]. An FDA-approved companion diagnostic for the detection of PD-L1 in patients with unresectable or metastatic HER2-negative gastric or gastroesophageal junction adenocarcinoma (G/GEJ) is not available.

2.2 Recommended Dosage

The recommended dosages of TEVIMBRA administered intravenously as a single agent or in combination with other therapeutic agents are presented in Table 1.

Table 1: Recommended Dosages for TEVIMBRA as a Single Agent or in Combination with Other Therapeutic Agents
Indication | Recommended Dosage of TEVIMBRA | Duration/Timing of Treatment
ESCC OR First-Line Gastric Cancer | 150 mg every 2 weeks OR 200 mg every 3 weeks OR 300 mg every 4 weeks OR 400 mg every 6 weeks | Until disease progression or unacceptable toxicity.

Refer to the respective Prescribing Information for each therapeutic agent administered in combination with TEVIMBRA for the recommended dosage information, as appropriate.

2.3 Dosage Modifications for Adverse Reactions

No dose reduction of TEVIMBRA is recommended. In general, withhold TEVIMBRA for severe (Grade 3) immune-mediated adverse reactions. Permanently discontinue TEVIMBRA for life-threatening (Grade 4) immune-mediated adverse reactions, recurrent severe (Grade 3) immune-mediated reactions that require systemic immunosuppressive treatment, or an inability to reduce corticosteroid dose to 10 mg or less of prednisone equivalent per day within 12 weeks of initiating steroids [see Warnings and Precautions (5.1)].

Dosage modifications for TEVIMBRA for adverse reactions that require management different from these general guidelines are summarized in Table 2.

Refer to the respective Prescribing Information for dosage modifications for the platinum and fluoropyrimidine agent administered in combination with TEVIMBRA.

Table 2: Recommended Dosage Modifications for Adverse Reactions
Adverse Reaction | Severity of Adverse Reaction [Based on Common Terminology Criteria for Adverse Events (CTCAE) Version 4.] | Dosage Modifications
Immune-Mediated Adverse Reactions [see Warnings and Precautions (5.1)]
Pneumonitis | Grade 2 | Withhold [Resume in patients with complete or partial resolution (Grades 0 to 1) after corticosteroid taper. Permanently discontinue if no complete or partial resolution within 12 weeks of initiating steroids or inability to reduce prednisone to 10 mg per day or less (or equivalent) within 12 weeks of initiating steroids.]
Pneumonitis | Grade 3 or 4 or recurrent Grade 2 | Permanently discontinue
Colitis | Grade 2 or 3 | Withhold
Colitis | Grade 4 | Permanently discontinue
Hepatitis with no tumor involvement of the liver | AST or ALT increases to more than 3 and up to 8 times ULN or Total bilirubin increases to more than 1.5 and up to 3 times ULN | Withhold
Hepatitis with no tumor involvement of the liver | AST or ALT increases to more than 8 times ULN or Total bilirubin increases to more than 3 times ULN | Permanently discontinue
Hepatitis with tumor involvement of the liver [If AST and ALT are less than or equal to ULN at baseline, withhold or permanently discontinue TEVIMBRA based on recommendations for hepatitis with no liver involvement.] | Baseline AST or ALT is more than 1 and up to 3 times ULN and increases to more than 5 and up to 10 times ULN or Baseline AST or ALT is more than 3 and up to 5 times ULN and increases to more than 8 and up to 10 times ULN | Withhold
Hepatitis with tumor involvement of the liver [If AST and ALT are less than or equal to ULN at baseline, withhold or permanently discontinue TEVIMBRA based on recommendations for hepatitis with no liver involvement.] | ALT or AST increases to more than 10 times ULN or Total bilirubin increases to more than 3 times ULN | Permanently discontinue
Endocrinopathies | Grade 3 or 4 | Withhold until clinically stable or permanently discontinue depending on severity
Nephritis with renal dysfunction | Grade 2 or 3 increased blood creatinine | Withhold
Nephritis with renal dysfunction | Grade 4 increased blood creatinine | Permanently discontinue
Exfoliative dermatologic conditions | Grade 3, or suspected SJS, TEN, or DRESS | Withhold
Exfoliative dermatologic conditions | Grade 4, or confirmed SJS, TEN, or DRESS | Permanently discontinue
Myocarditis | Grade 2, 3, or 4 | Permanently discontinue
Neurological toxicities | Grade 2 | Withhold
Neurological toxicities | Grade 3 or 4 | Permanently discontinue
Other Adverse Reactions
Infusion-related reactions [see Warnings and Precautions (5.2)] | Grade 1 | Slow infusion rate by 50%
Infusion-related reactions [see Warnings and Precautions (5.2)] | Grade 2 | Interrupt infusion [Resume infusion if resolved or decreased to Grade 1, and slow rate of infusion by 50% of the previous rate.]
 | Grade 3 or 4 | Permanently discontinue
ALT = alanine aminotransferase, AST = aspartate aminotransferase, ULN = upper limit of normal, SJS = Stevens-Johnson syndrome, TEN = toxic epidermal necrolysis, DRESS = drug rash with eosinophilia and systemic symptoms.

2.4 Preparation and Administration

Preparation

Parenteral drug products should be inspected visually for particulate matter and discoloration prior to administration, whenever solution and container permit. TEVIMBRA is a clear to slightly opalescent, colorless to slightly yellow solution. Discard the vial if the solution is cloudy, discolored, or contains visible particles. Do not shake the vial.

Prepare the solution for infusion as follows:

- Withdraw the required volume of TEVIMBRA from the vial(s).
- Transfer solution into an intravenous infusion bag containing 0.9% Sodium Chloride Injection, USP to prepare an infusion solution with a final concentration of 2 mg/mL to 5 mg/mL.
- Mix diluted solution by gentle inversion to avoid foaming or excessive shearing of the solution. Do not shake.
- TEVIMBRA is for single use only. Discard any unused portion left in the vial.

Storage of Diluted Solution

This product does not contain any preservatives. If not used immediately, store the TEVIMBRA diluted solution either:

- At room temperature at 20°C to 25°C (68°F to 77°F) for up to 4 hours, including preparation and infusion duration. Discard after 4 hours.
- Under refrigeration at 2°C to 8°C (36°F to 46°F) for up to 10 days (240 hours), including preparation and infusion duration. Allow the diluted solution to come to room temperature prior to administration. Discard after 10 days (240 hours).

Protect diluted solution from light during storage. Do not freeze the diluted solution.

Administration

- Administer diluted solution by intravenous infusion through an intravenous line with a sterile, nonpyrogenic, low protein binding 0.2 micron or 0.22 micron in-line or add-on filter.
- For 150 mg and 200 mg doses, administer the initial infusion over 60 minutes. If tolerated, all subsequent infusions may be administered over 30 minutes.
  For 300 mg doses, administer the initial infusion over 90 minutes. If tolerated, administer the second infusion over 60 minutes. If the second infusion is tolerated, administer subsequent infusions over 30 minutes.
  For 400 mg doses, administer the initial infusion over 120 minutes. If tolerated, administer the second infusion over 60 minutes. If the second infusion is tolerated, administer subsequent infusions over 30 minutes.
- Do NOT coadminister other drugs through the same infusion line.
- Do NOT administer TEVIMBRA as an intravenous push or single bolus injection.
- Flush the intravenous line at the end of infusion.

3 DOSAGE FORMS AND STRENGTHS

Injection: 100 mg/10 mL (10 mg/mL) clear to slightly opalescent, colorless to slightly yellow solution in a single-dose vial.

4 CONTRAINDICATIONS

None.

5 WARNINGS AND PRECAUTIONS

5.1 Severe and Fatal Immune-Mediated Adverse Reactions

TEVIMBRA is a monoclonal antibody that belongs to a class of drugs that bind to either the programmed death receptor-1 (PD-1) or PD-ligand 1 (PD-L1), blocking the PD-1/PD-L1 pathway, thereby removing inhibition of the immune response, potentially breaking peripheral tolerance and inducing immune-mediated adverse reactions. Important immune-mediated adverse reactions listed under WARNINGS AND PRECAUTIONS may not include all possible severe and fatal immune-mediated reactions.

Immune-mediated adverse reactions, which may be severe or fatal, can occur in any organ system or tissue. Immune-mediated adverse reactions can occur at any time after starting treatment with a PD-1/PD-L1 blocking antibody. While immune-mediated adverse reactions usually manifest during treatment with PD-1/PD-L1 blocking antibodies, immune-mediated adverse reactions can also manifest after discontinuation of PD-1/PD-L1 blocking antibodies.

Early identification and management of immune-mediated adverse reactions are essential to ensure safe use of PD-1/PD-L1 blocking antibodies. Monitor patients closely for symptoms and signs that may be clinical manifestations of underlying immune-mediated adverse reactions. Evaluate liver enzymes, creatinine, and thyroid function at baseline and periodically during treatment. In cases of suspected immune-mediated adverse reactions, initiate appropriate workup to exclude alternative etiologies, including infection. Institute medical management promptly, including specialty consultation as appropriate.

Withhold or permanently discontinue TEVIMBRA depending on severity [see Dosage and Administration (2.2)]. In general, if TEVIMBRA requires interruption or discontinuation, administer systemic corticosteroid therapy (1 to 2 mg/kg/day prednisone or equivalent) until improvement to Grade 1 or less. Upon improvement to Grade 1 or less, initiate corticosteroid taper and continue to taper over at least 1 month. Consider administration of other systemic immunosuppressants in patients whose immune-mediated adverse reactions are not controlled with corticosteroids.

Toxicity management guidelines for adverse reactions that do not necessarily require systemic steroids (e.g., endocrinopathies and dermatologic reactions) are discussed below.

Immune-Mediated Pneumonitis

TEVIMBRA can cause immune-mediated pneumonitis, which can be fatal. In patients treated with other PD-1/PD-L1 blocking antibodies, the incidence of pneumonitis is higher in patients who have received prior thoracic radiation.

Immune-mediated pneumonitis occurred in 4.7% (113/2390) of patients receiving TEVIMBRA, including fatal (0.1%), Grade 4 (0.3%), Grade 3 (1.4%), and Grade 2 (1.9%) adverse reactions. Pneumonitis led to permanent discontinuation of TEVIMBRA in 44 (1.8%) patients and withholding of TEVIMBRA in 40 (1.7%) patients.

Eighty-one (71.7%) of the 113 patients received systemic corticosteroids. Seventy-four (65.5%) of the 113 patients received high-dose systemic corticosteroids. Immune-mediated pneumonitis resolved in 48.7% of the 113 patients. Of the 40 patients in whom TEVIMBRA was withheld for pneumonitis, 26 (65%) reinitiated TEVIMBRA after symptom improvement; of these, 5 (19%) patients had recurrence of pneumonitis.

Immune-Mediated Colitis

TEVIMBRA can cause immune-mediated colitis, which can be fatal. Cytomegalovirus infection/reactivation has been reported in patients with corticosteroid-refractory immune-mediated colitis treated with PD-1/PD-L1 blocking antibodies. In cases of corticosteroid-refractory colitis, consider repeating infectious workup to exclude alternative etiologies.

Immune-mediated colitis occurred in 0.8% (19/2390) of patients receiving TEVIMBRA, including Grade 3 (0.3%) and Grade 2 (0.4%) adverse reactions. Colitis led to permanent discontinuation of TEVIMBRA in 5 (0.2%) patients and withholding of TEVIMBRA in 10 (0.4%) patients. Seventeen (89.5%) of the 19 patients received systemic corticosteroids. Twelve (63.2%) of the 19 patients received high-dose systemic corticosteroids. Two (10.5%) of the 19 patients received immunosuppressive treatment. Immune-mediated colitis resolved in 89.5% of the 19 patients. Of the 10 patients in whom TEVIMBRA was withheld for colitis, 9 (90%) reinitiated TEVIMBRA after symptom improvement; of these, 2 (22%) patients had recurrence of colitis.

Immune-Mediated Hepatitis

TEVIMBRA can cause immune-mediated hepatitis, which can be fatal.

Immune-mediated hepatitis occurred in 1.3% (30/2390) of patients receiving TEVIMBRA, including Grade 4 (0.3%), Grade 3 (0.6%), and Grade 2 (0.3%) adverse reactions. Immune-mediated hepatitis led to permanent discontinuation in 6 (0.3%) patients and withholding of TEVIMBRA in 19 (0.8%) patients. Twenty-five (83.3%) of the 30 patients received systemic corticosteroids. Twenty-four (80%) of the 30 patients received high-dose systemic corticosteroids. Two (6.7%) of the 30 patients received immunosuppressive treatment. Immune-mediated hepatitis resolved in 66.7% of the 30 patients. Of the 19 patients in whom TEVIMBRA was withheld for hepatitis, 7 (37%) reinitiated TEVIMBRA after symptom improvement; of these, 1 (14%) patient had recurrence of hepatitis.

Immune-Mediated Endocrinopathies

Adrenal Insufficiency

TEVIMBRA can cause immune-mediated adrenal insufficiency. For Grade 2 or higher adrenal insufficiency, initiate symptomatic treatment, including hormone replacement as clinically indicated. Withhold TEVIMBRA depending on severity [see Dosage and Administration (2.2)].

Immune-mediated adrenal insufficiency occurred in 0.5% (12/2390) of patients receiving TEVIMBRA, including Grade 4 (0.04%), Grade 3 (0.2%), and Grade 2 (0.3%) adverse reactions. Adrenal insufficiency did not lead to permanent discontinuation of TEVIMBRA. TEVIMBRA was withheld in 10 (0.4%) patients. All 12 patients received systemic corticosteroids. Three (25%) of the 12 patients received high-dose systemic corticosteroids. Adrenal insufficiency resolved in 25% of the 12 patients. Of the 10 patients in whom TEVIMBRA was withheld for adrenal insufficiency, 8 (80%) reinitiated TEVIMBRA after symptom improvement; of these, none of the patients had recurrence of adrenal insufficiency.

Hypophysitis

TEVIMBRA can cause immune-mediated hypophysitis. Hypophysitis can present with acute symptoms associated with mass effect such as headache, photophobia, or visual field defects. Hypophysitis can cause hypopituitarism. Initiate hormone replacement as clinically indicated. Withhold or permanently discontinue TEVIMBRA depending on severity [see Dosage and Administration (2.2)].

Hypophysitis/hypopituitarism occurred in 0.3% (6/2390) of patients receiving TEVIMBRA; all were Grade 2 (0.3%). Hypophysitis did not lead to permanent discontinuation of TEVIMBRA. TEVIMBRA was withheld in 1 (0.04%) patient. Five (83.3%) of the 6 patients received systemic corticosteroids. One (17%) of the 6 patients received high-dose systemic corticosteroids. Hypophysitis/hypopituitarism resolved in 17% of the 6 patients. For the 1 patient where TEVIMBRA was withheld for hypophysitis/hypopituitarism, there was no recurrence of hypophysitis/hypopituitarism.

Thyroid Disorders

TEVIMBRA can cause immune-mediated thyroid disorders. Thyroiditis can present with or without endocrinopathy. Hypothyroidism can follow hyperthyroidism. Initiate hormone replacement for hypothyroidism or institute medical management of hyperthyroidism as clinically indicated. Withhold or permanently discontinue TEVIMBRA depending on severity [see Dosage and Administration (2.2)].

Thyroiditis: Immune-mediated thyroiditis occurred in 1% (25/2390) of patients receiving TEVIMBRA, including Grade 2 (0.5%) adverse reactions. Thyroiditis did not lead to permanent discontinuation of TEVIMBRA. TEVIMBRA was withheld in 5 (0.2%) patients. Two (8%) of the 25 patients received systemic corticosteroids. Thyroiditis resolved in 36% of the 25 patients. All 5 patients in whom TEVIMBRA was withheld for thyroiditis reinitiated TEVIMBRA after symptom improvement; of these, 1 (20%) patient had recurrence of thyroiditis.

Hyperthyroidism: Immune-mediated hyperthyroidism occurred in 4.9% (118/2390) of patients receiving TEVIMBRA, including Grade 3 (0.04%) and Grade 2 (0.9%) adverse reactions. Hyperthyroidism led to the permanent discontinuation of TEVIMBRA in 1 (0.04%) patient and withholding of TEVIMBRA in 7 (0.3%) patients. Three (2.5%) of the 118 patients received systemic corticosteroids. Hyperthyroidism resolved in 76.3% of the 118 patients. Of the 7 patients in whom TEVIMBRA was withheld for hyperthyroidism, 5 (71.4%) reinitiated TEVIMBRA after symptom improvement; of these, none of the patients had recurrence of hyperthyroidism.

Hypothyroidism: Immune-mediated hypothyroidism occurred in 12.5% (299/2390) of patients receiving TEVIMBRA, including Grade 4 (0.04%), Grade 3 (0.04%), and Grade 2 (6.7%) adverse reactions. TEVIMBRA was permanently discontinued in 2 (0.1%) patients and treatment was withheld in 12 (0.5%) patients. Two (0.7%) of the 299 patients received systemic corticosteroids. One hundred ninety-five patients received hormone replacement therapy. Hypothyroidism resolved in 34.4% of the 299 patients. The majority (83.6%) of patients with hypothyroidism required long-term thyroid hormone replacement. Of the 12 patients in whom TEVIMBRA was withheld for hypothyroidism, 11 (91.7%) reinitiated TEVIMBRA after symptom improvement; of these, 2 (18.2%) patients had recurrence of hypothyroidism.

Type 1 Diabetes Mellitus, Which Can Present with Diabetic Ketoacidosis

Diabetes mellitus has been reported with PD-1/PD-L1 blocking antibodies. Monitor patients for hyperglycemia or other signs and symptoms of diabetes. Initiate treatment with insulin as clinically indicated. Withhold or permanently discontinue TEVIMBRA depending on severity [see Dosage and Administration (2.2)].

Diabetes mellitus occurred in 0.7% (16/2390) of patients receiving TEVIMBRA, including Grade 4 (0.1%), Grade 3 (0.3%), and Grade 2 (0.3%) adverse reactions. TEVIMBRA was permanently discontinued in 4 (0.2%) patients, and TEVIMBRA treatment was withheld in 4 (0.2%) patients. Fourteen of the 16 patients received insulin therapy for diabetes mellitus. Diabetes mellitus resolved in 12.5% of the 16 patients. Of the 4 patients in whom TEVIMBRA was withheld for diabetes mellitus, 1 (25%) patient reinitiated TEVIMBRA after symptom improvement.

Immune-Mediated Nephritis with Renal Dysfunction

TEVIMBRA can cause immune-mediated nephritis, which can be fatal.

Immune-mediated nephritis with renal dysfunction occurred in 0.2% (5/2390) of patients receiving TEVIMBRA, including Grade 3 (0.04%) and Grade 2 (0.1%) adverse reactions. TEVIMBRA was permanently discontinued in 1 (0.04%) patient and treatment was withheld in 3 (0.1%) patients. Three (60%) out of 5 patients received systemic corticosteroids. Three (60%) of the 5 patients received high-dose systemic corticosteroids. Nephritis with renal dysfunction resolved in 40% of the 5 patients. Of the 3 patients in whom TEVIMBRA was withheld for nephritis, 2 (66.7%) reinitiated TEVIMBRA after symptom improvement and no patients had recurrence of nephritis.

Immune-Mediated Dermatologic Adverse Reactions

TEVIMBRA can cause immune-mediated rash or dermatitis. Cases of severe cutaneous adverse reactions (SCARs), including exfoliative dermatitis, Stevens-Johnson syndrome (SJS), and toxic epidermal necrolysis (TEN), have been reported, some with fatal outcome. Topical emollients and/or topical corticosteroids may be adequate to treat mild to moderate non-exfoliative rashes. Withhold or permanently discontinue TEVIMBRA depending on severity [see Dosage and Administration (2.2)].

Immune-mediated dermatologic adverse reactions occurred in 13% (311/2390) of patients receiving TEVIMBRA, including Grade 4 (0.1%), Grade 3 (1.1%), and Grade 2 (3.4%) adverse reactions. Stevens-Johnson syndrome occurred in 1 (0.04%) patient. Dermatologic adverse reactions led to permanent discontinuation of TEVIMBRA in 3 (0.1%) patients and withholding of TEVIMBRA in 30 (1.3%) patients. Forty-four (14.1%) of the 311 patients received systemic corticosteroids. Nineteen (6.1%) of the 311 patients received high-dose systemic corticosteroids. Immune-mediated skin reactions resolved in 66.9% of the 311 patients. Of the 30 patients in whom TEVIMBRA was withheld for dermatologic adverse reactions, 26 (86.7%) reinitiated TEVIMBRA after symptom improvement; of these, 3 (12%) patients had recurrence of immune-mediated dermatologic adverse reactions.

Other Immune-Mediated Adverse Reactions

The following clinically significant immune-mediated adverse reactions occurred at an incidence of less than 1% in 2390 patients who received TEVIMBRA or were reported with the use of other PD-1/PD-L1 blocking antibodies. Severe or fatal cases have been reported for some of these adverse reactions.

Cardiac/Vascular: Myocarditis, pericarditis, vasculitis.

Nervous System: Meningitis, encephalitis, myelitis and demyelination, myasthenic syndrome/myasthenia gravis (including exacerbation), Guillain-Barre syndrome, nerve paresis, autoimmune neuropathy.

Ocular: Uveitis, iritis, and other ocular inflammatory toxicities. Some cases can be associated with retinal detachment. Various grades of visual impairment, including blindness, can occur. If uveitis occurs in combination with other immune-mediated adverse reactions, consider a Vogt-Koyanagi-Harada–like syndrome, as this may require treatment with systemic steroids to reduce the risk of permanent vision loss.

Gastrointestinal: Pancreatitis including increases in serum amylase and lipase levels, gastritis, duodenitis, stomatitis.

Musculoskeletal and Connective Tissue: Myositis/polymyositis/dermatomyositis, rhabdomyolysis and associated sequelae including renal failure, arthritis, polymyalgia rheumatica.

Endocrine: Hypoparathyroidism.

Other (Hematologic/Immune): Hemolytic anemia, aplastic anemia, hemophagocytic lymphohistiocytosis, systemic inflammatory response syndrome, histiocytic necrotizing lymphadenitis (Kikuchi lymphadenitis), sarcoidosis, immune thrombocytopenia, solid organ transplant rejection, other transplant (including corneal graft) rejection.

5.2 Infusion-Related Reactions

TEVIMBRA can cause severe or life-threatening infusion-related reactions. Infusion-related reactions occurred in 4.7% (113/2390) patients receiving TEVIMBRA, including Grade 3 or higher (0.2%) reactions. Monitor patients for signs and symptoms of infusion-related reactions.

Slow the rate of infusion for mild (Grade 1) and interrupt the infusion for moderate (Grade 2) infusion-related reactions. For severe (Grade 3) or life-threatening (Grade 4) infusion-related reactions, stop infusion and permanently discontinue TEVIMBRA [see Dosage and Administration (2.2)].

5.3 Complications of Allogeneic HSCT

Fatal and other serious complications can occur in patients who receive allogeneic hematopoietic stem cell transplantation (HSCT) before or after being treated with a PD-1/PD-L1 blocking antibody. Transplant-related complications include hyperacute graft-versus-host disease (GVHD), acute GVHD, chronic GVHD, hepatic veno-occlusive disease after reduced intensity conditioning, and steroid-requiring febrile syndrome (without an identified infectious cause). These complications may occur despite intervening therapy between PD-1/PD-L1 blockade and allogeneic HSCT.

Follow patients closely for evidence of transplant-related complications and intervene promptly. Consider the benefit versus risks of treatment with a PD-1/PD-L1 blocking antibody prior to or after an allogeneic HSCT.

5.4 Embryo-Fetal Toxicity

Based on its mechanism of action, TEVIMBRA can cause fetal harm when administered to a pregnant woman. Animal studies have demonstrated that inhibition of the PD-1/PD-L1 pathway can lead to increased risk of immune-mediated rejection of the developing fetus resulting in fetal death. Advise pregnant women of the potential risk to a fetus. Advise females of reproductive potential to use effective contraception during treatment with TEVIMBRA and for 4 months after the last dose [see Use in Specific Populations (8.1, 8.3)].

6 ADVERSE REACTIONS

The following clinically significant adverse reactions are discussed in more detail in other sections of the label:

- Severe and fatal immune-mediated adverse reactions [see Warnings and Precautions (5.1)]
- Infusion-related reactions [see Warnings and Precautions (5.2)]

6.1 Clinical Trials Experience

Because clinical trials are conducted under widely varying conditions, adverse reaction rates observed in the clinical trials of a drug cannot be directly compared to rates in the clinical trials of another drug and may not reflect the rates observed in practice.

The pooled safety population described in WARNINGS AND PRECAUTIONS reflect exposure to TEVIMBRA as a single agent in 2390 patients enrolled in three randomized open-label, active-controlled studies (BGB-A317-301, RATIONALE-302, BGB-A317-303) and six open-label, single-arm studies (BGB-A317-209, BGB-A317-208, BGB-A317-204, BGB-A317-203, BGB-A317-102, BGB-A317_Study_001), which enrolled 307 patients with esophageal squamous cell carcinoma and 2083 patients with advanced or recurrent tumors. TEVIMBRA was administered at a dose of 200 mg intravenously once every 3 weeks, except in study BGB-A317_Study_001 where patients also received other dosage regimens. Among the 2390 patients, 38% were exposed for longer than 6 months, and 23% were exposed for longer than 12 months.

First-line Treatment of Unresectable or Metastatic Esophageal Carcinoma (ESCC)

The safety of TEVIMBRA in combination with chemotherapy was evaluated in RATIONALE-306, a randomized, placebo-controlled, multicenter, double-blind trial in patients with unresectable, advanced, or metastatic ESCC [see Clinical Studies (14.1)].

Patients were randomized (1:1) to receive either TEVIMBRA 200 mg by intravenous infusion over 30-60 minutes every 3 weeks or placebo plus a chemotherapy doublet regimen. The chemotherapy doublet regimens consisted of:

- Platinum (cisplatin [60 to 80 mg/m^2 IV, on Day 1] or oxaliplatin [130 mg/m^2 IV, on Day 1]) and a fluoropyrimidine (5-FU [750 to 800 mg/m^2 IV, on Day 1 to 5] or capecitabine [1000 mg/m^2 orally twice daily, on Day 1 to 14])

or

- Platinum (cisplatin [60 to 80 mg/m^2 IV, on Day 1 or 2] or oxaliplatin [130 mg/m^2 IV, on Day 1 or 2]) and (paclitaxel 175 mg/m^2 IV, on Day 1)

Patients were treated until disease progression or unacceptable toxicity. The median duration of exposure was 6.4 months (range: 0.1 to 38.3 months) in TEVIMBRA-treated patients.

Serious adverse reactions occurred in 48% of patients receiving TEVIMBRA in combination with chemotherapy. The most frequent serious adverse reactions (≥2%) were pneumonia (5.2%), dysphagia (5.2%), diarrhea (2.2%), fatigue (2.2%), and esophageal stenosis (2.2%). Fatal adverse reactions occurred in 8% of patients who received TEVIMBRA in combination with chemotherapy.

Permanent discontinuation of TEVIMBRA due to adverse reactions occurred in 13% of patients. The adverse reaction which resulted in discontinuation in ≥2% of patients was pneumonitis (2.2%).

Dosage interruptions of TEVIMBRA due to adverse reactions occurred in 52% of patients. Adverse reactions which required dosage interruption in ≥2% of patients were neutrophil count decreased (7%), fatigue (6%), pneumonia (6%), anemia (4.3%), neutropenia (4.3%), white blood cell count decreased (4.3%), rash (3.7%), dysphagia (2.8%), platelet count decreased (2.8%), pyrexia (2.8%), and diarrhea (2.2%).

The most common (≥20%) adverse reactions including laboratory abnormalities were decreased neutrophil count, decreased sodium, increased glucose, anemia, fatigue, decreased appetite, increased AST, decreased potassium, increased serum creatinine, decreased calcium, increased ALT, diarrhea, stomatitis, and vomiting.

Adverse reactions and laboratory abnormalities are listed in Table 3 and Table 4, respectively.

Table 3: Adverse Reactions (≥10%) in Patients with ESCC Receiving TEVIMBRA + Chemotherapy with a Difference Between Arms of ≥5% for All Grades or ≥2% for Grades 3 and 4 vs Placebo + Chemotherapy in RATIONALE-306
Adverse Reaction | TEVIMBRA + Chemotherapy N=324 |  | Placebo + Chemotherapy N=321
Adverse Reaction | All Grades (%) | Grade 3 or 4 (%) | All Grades (%) | Grade 3 or 4 (%)
Blood and Lymphatic System Disorders
Anemia | 61 | 17 | 56 | 16
Neutropenia | 16 | 7 | 15 | 10
General Disorders and Administration Site Conditions
Fatigue [Represents a composite of multiple, related preferred terms.] | 45 | 9 | 45 | 4.7
Metabolism and Nutrition Disorders
Decreased Appetite | 44 | 6 | 39 | 2.2
Gastrointestinal Disorders
Diarrhea | 28 | 4.3 | 24 | 1.9
Stomatitis | 22 | 4 | 16 | 2.2
Vomiting | 22 | 1.5 | 27 | 2.5
Dysphagia | 14 | 6 | 11 | 4
Skin and Subcutaneous Tissue Disorders
Rash | 19 | 4 | 9 | 0.3
Pruritus | 13 | 0.3 | 7 | 0
Endocrine Disorders
Hypothyroidism | 11 | 0 | 6 | 0

Table 4: Select Laboratory Abnormalities Worsening From Baseline Occurring in ≥10% of Patients Receiving TEVIMBRA in Combination with Chemotherapy in RATIONALE-306 with a Difference Between Arms of ≥5% for All Grades or ≥2% for Grades 3 and 4 vs Placebo + Chemotherapy in RATIONALE-306
Laboratory Abnormality | TEVIMBRA + Chemotherapy [The denominator used to calculate the rate varied from 132 to 323 based on the number of patients with a baseline value and at least one post-treatment value.] (N=324) |  | Placebo + Chemotherapy (N=321)
Laboratory Abnormality | All Grades (%) | Grade 3 or 4 (%) | All Grades (%) | Grade 3 or 4 (%)
Hematology
Neutrophils decreased | 75 | 41 | 75 | 46
Chemistry
Sodium decreased | 67 | 19 | 62 | 11
Glucose increased | 65 | 7 | 61 | 5
AST increased | 36 | 3.4 | 27 | 1.3
Potassium decreased | 33 | 10 | 29 | 2.8
Creatinine increased | 33 | 2.5 | 25 | 1.6
Calcium decreased | 29 | 6 | 24 | 4.4
ALT increased | 28 | 3.1 | 22 | 1.6

Previously Treated Unresectable Advanced or Metastatic Esophageal Squamous Cell Carcinoma (ESCC)

The safety of TEVIMBRA was evaluated in RATIONALE-302, a randomized, active-controlled, open-label, multicenter study in 255 patients with unresectable advanced, recurrent or metastatic ESCC [see Clinical Studies (14.1)]. The trial excluded patients who had brain or leptomeningeal metastases that were symptomatic or required treatment, active autoimmune disease, a medical condition requiring systemic corticosteroids or immunosuppressants, or apparent tumor invasion of organs adjacent to the esophageal site.

Patients received TEVIMBRA 200 mg by intravenous infusion over 30-60 minutes every 3 weeks or investigator's choice: paclitaxel 135-175 mg/m^2 every 3 weeks or 80-100 mg/m^2 weekly, docetaxel 75 mg/m^2 every 3 weeks, or irinotecan 125 mg/m^2 on Days 1 and 8 of every 3-week cycle. Patients were treated until disease progression or unacceptable toxicity. The median duration of exposure was 2.8 months (range: 0.2 to 28.3 months) in TEVIMBRA-treated patients and 1.5 months (range: 0.2 to 19.2 months) in paclitaxel, docetaxel, or irinotecan-treated patients.

Serious adverse reactions occurred in 41% of patients; the most frequent serious adverse reactions (≥2%) were pneumonia, dysphagia, hemorrhage, pneumonitis (including pneumonitis and immune-mediated pneumonitis), and esophageal obstruction. Fatal adverse reactions occurred in 7% of patients who received TEVIMBRA, including the following which occurred in more than one patient: pneumonia/pneumonitis (5 patients), hemorrhage (3 patients), and death due to an unknown cause (3 patients).

Permanent discontinuation of TEVIMBRA due to an adverse reaction occurred in 19% of patients. Adverse reactions which resulted in permanent discontinuation in ≥1% of patients were hemorrhage, pneumonitis (including pneumonitis and immune-mediated pneumonitis), and pneumonia.

Dosage interruptions of TEVIMBRA due to an adverse reaction occurred in 23% of patients. Adverse reactions which required dosage interruptions in ≥2% of patients were pneumonia, pneumonitis, and fatigue.

The most common (≥20%) adverse reactions were anemia, fatigue, musculoskeletal pain, decreased weight, and cough.

Adverse reactions and laboratory abnormalities are listed in Table 5 and Table 6, respectively.

Table 5: Adverse Reactions (≥10%) in Patients With ESCC Receiving TEVIMBRA in RATIONALE-302
Adverse Reaction | TEVIMBRA (N=255) |  | ICC (N=240)
Adverse Reaction | All Grades (%) | Grade 3 or 4 (%) | All Grades (%) | Grade 3 or 4 (%)
Blood Disorders
Anemia | 31 | 6 | 45 | 11
General Disorders
Fatigue [Fatigue includes asthenia, fatigue, malaise.] | 28 | 2 | 46 | 6
Pyrexia | 16 | 0.4 | 14 | 0
Musculoskeletal and Connective Tissue Disorders
Musculoskeletal pain [Musculoskeletal pain includes musculoskeletal pain, spinal pain, arthralgia, back pain, neck pain, musculoskeletal chest pain, myalgia, pain in extremity, non-cardiac chest pain, bone pain, arthritis.] | 24 | 1 | 25 | 1
Investigations
Weight decreased | 23 | 1 | 19 | 0
Respiratory, Thoracic and Mediastinal Disorders
Cough [Cough includes productive cough, cough.] | 22 | 0.4 | 16 | 0.4
Metabolism and Nutrition Disorders
Decreased appetite | 16 | 0.4 | 35 | 4
Infections and Infestations
Pneumonia [Pneumonia includes pneumonia aspiration, pneumonia, pneumonia bacterial, lower respiratory tract infection.] | 16 | 6 | 12 | 7
Gastrointestinal Disorders
Constipation | 15 | 0 | 19 | 0.4
Nausea | 14 | 0.4 | 30 | 3
Diarrhea [Diarrhea includes diarrhea, colitis.] | 13 | 1 | 32 | 7
Dysphagia | 11 | 6 | 8 | 3
Abdominal pain [Abdominal pain includes abdominal pain upper, abdominal pain, abdominal discomfort, abdominal pain lower, gastrointestinal pain.] | 11 | 0.8 | 16 | 2
Vomiting | 11 | 0.8 | 20 | 4
Endocrine Disorders
Hypothyroidism [Hypothyroidism includes hypothyroidism, blood thyroid stimulating hormone increased.] | 13 | 0.4 | 0.8 | 0
Skin and Subcutaneous Tissue Disorders
Rash [Rash includes dermatitis, dermatitis acneiform, dermatitis allergic, eczema, erythema, psoriasis, rash, rash follicular, rash maculo-papular, rash pruritic.] | 13 | 0.4 | 6 | 0
Vascular Disorders
Hemorrhage [Hemorrhage includes tumor hemorrhage, upper gastrointestinal hemorrhage, gastrointestinal hemorrhage, hemoptysis, esophageal hemorrhage, hematuria, gastric hemorrhage, epistaxis, tracheal hemorrhage, gingival bleeding, pulmonary hemorrhage, procedural hemorrhage, rectal hemorrhage, stoma site hemorrhage.] | 12 | 2 | 10 | 3
ICC = investigator's choice of chemotherapy

Table 6: Laboratory Abnormalities Worsening From Baseline Occurring in ≥10% of Patients Receiving TEVIMBRA in RATIONALE-302
 | TEVIMBRA [The denominator used to calculate the rate varied from 136 to 240 based on the number of patients with a baseline value and at least one post-treatment value.] |  | ICC
Laboratory Abnormality | All Grades (%) | Grade 3 or 4 (%) | All Grades (%) | Grade 3 or 4 (%)
Chemistry
Glucose increased | 46 | 4 | 40 | 2
Sodium decreased | 34 | 9 | 36 | 8
Albumin decreased | 33 | 0.8 | 37 | 1
Alkaline phosphatase increased | 32 | 3 | 15 | 0.5
AST increased | 27 | 0.8 | 12 | 0.5
ALT increased | 23 | 0.8 | 15 | 1
Phosphate decreased | 15 | 4 | 20 | 3
Creatine kinase increased | 13 | 1 | 2 | 0
Potassium decreased | 13 | 1 | 15 | 3
Bilirubin increased | 11 | 2 | 8 | 0.5
Glucose decreased | 10 | 0.4 | 10 | 0.5
Hematology
Hemoglobin decreased | 45 | 6 | 61 | 10
Lymphocytes decreased | 43 | 11 | 60 | 28
Platelets decreased | 11 | 1 | 11 | 0.9
Leukocytes decreased | 10 | 0.8 | 66 | 31

Treatment of Previously Untreated Unresectable or Metastatic Gastric or Gastroesophageal Junction Adenocarcinoma (G/GEJ)

The safety of TEVIMBRA in combination with chemotherapy was evaluated in RATIONALE-305, a randomized, multicenter, double-blind, placebo-controlled trial in patients with previously untreated unresectable or metastatic G/GEJ adenocarcinoma [see Clinical Studies (14.2)].

Patients were randomized (1:1) to receive either TEVIMBRA 200 mg by intravenous infusion over 30-60 minutes every 3 weeks or placebo plus a platinum and fluoropyrimidine-based chemotherapy. The chemotherapy regimens consisted of:

- Oxaliplatin 130 mg/m^2 IV on Day 1 for up to 6 cycles and capecitabine 1000 mg/m^2 orally twice daily for 14 consecutive days of every 3-week cycle

or

- Cisplatin 80 mg/m^2 IV, Day 1, and 5-FU (5-fluorouracil) 800 mg/m^2/day IV continuous infusion over 24 hours daily Day 1-5, every 3 weeks for up to 6 cycles

Patients were treated until disease progression or unacceptable toxicity. The median duration of exposure was 5.91 months (range: 0.1 to 47 months) in TEVIMBRA-treated patients.

Serious adverse reactions occurred in 42% of patients receiving TEVIMBRA in combination with chemotherapy. The most frequent serious adverse drug reactions (≥2%) were pneumonia (3.6%), decreased platelet count (3.2%), gastrointestinal hemorrhage (3%), and colitis (2.2%). Fatal adverse reactions occurred in 4.2% of patients who received TEVIMBRA in combination with chemotherapy; events occurring in 2 or more patients were death, sepsis, pneumonia, pulmonary embolism, and respiratory failure.

Permanent discontinuation of TEVIMBRA due to an adverse reaction occurred in 16% of patients. Adverse drug reactions which resulted in permanent discontinuation in ≥1% of patients were death, fatigue, and pneumonitis.

Dosage interruption of TEVIMBRA due to an adverse drug reaction occurred in 49% of patients. Adverse drug reactions which required dosage interruption in ≥2% of patients were decreased platelet count (12%), decreased neutrophil count (10%), neutropenia (6%), decreased white blood cell count (6%), increased AST (4.8%), increased ALT (3.8%), increased blood bilirubin (3%), COVID-19 (3%), thrombocytopenia (2.8%), leukopenia (2.6%), pneumonitis (2.2%), and pneumonia (2%).

The most common (≥20%) adverse reactions, including laboratory abnormalities, for TEVIMBRA in combination with chemotherapy were nausea, fatigue, decreased appetite, anemia, peripheral sensory neuropathy, vomiting, decreased platelet count, decreased neutrophil count, increased aspartate aminotransferase, diarrhea, abdominal pain, increased alanine aminotransferase, white blood cell count decreased, decreased weight, and pyrexia.

Adverse reactions and laboratory abnormalities are listed in Table 7 and Table 8, respectively.

Table 7: Adverse Reactions (≥10%) in Patients with G/GEJ Receiving TEVIMBRA + Chemotherapy with a Difference Between Arms of ≥5% for All Grades or ≥2% for Grades 3 and 4 vs Placebo + Chemotherapy in RATIONALE-305
Adverse Drug Reaction | TEVIMBRA + Chemotherapy (N=498) |  | Placebo + Chemotherapy (N=494)
Adverse Drug Reaction | All Grades (%) | Grade 3 or 4 (%) | All Grades (%) | Grade 3 or 4 (%)
General Disorders and Administration Site Conditions
Pyrexia | 20 | 1.6 | 14 | 0.6
Skin and Subcutaneous Tissue Disorders
Rash [Represents a composite of multiple, related preferred terms.] | 16 | 1.6 | 7 | 0
Pruritus | 10 | 0.2 | 3.2 | 0
Endocrine Disorders
Hypothyroidism | 13 | 0.2 | 2.8 | 0

Other Clinically Important Adverse Reactions Occurring in Less Than 10% include:

Stomatitis, infusion-related reaction, dyspnea, hepatitis, hyperthyroidism, pneumonitis, hyperglycemia, myalgia, diabetes mellitus, pancreatitis, arthritis, Sjogren's syndrome, thyroiditis, adrenal insufficiency, hypophysitis, myasthenia gravis, uveitis, myocarditis, pericarditis, colitis, vitiligo, myositis, and nephritis.

Table 8: Select Laboratory Abnormalities Worsening from Baseline Occurring in ≥10% of Patients Receiving TEVIMBRA + Chemotherapy with a Difference Between Arms of ≥5% for All Grades or ≥2% for Grades 3 and 4 vs Placebo + Chemotherapy in RATIONALE-305
Laboratory Abnormality | TEVIMBRA + Chemotherapy [The denominator used to calculate the rate varied from 480 to 494 based on the number of patients with a baseline value and at least one post-treatment value.] (N=498) |  | Placebo + Chemotherapy (N=494)
Laboratory Abnormality | All Grades (%) | Grade 3 or 4 (%) | All Grades (%) | Grade 3 or 4 (%)
Chemistry
AST increased | 58 | 6 | 56 | 3
Sodium decreased | 42 | 7 | 36 | 5
ALT increased | 41 | 4.8 | 36 | 2
Potassium decreased | 33 | 9 | 28 | 6
Hematology
Lymphocytes decreased | 53 | 12 | 46 | 9
Abbreviations: ALT = alanine aminotransferase, AST = aspartate amino transferase.

Other Clinically Important Laboratory Abnormalities Occurring in <20% include:

Creatinine increased, potassium increased, glucose decreased, sodium increased, lymphocytes increased, hemoglobin increased.

6.2 Postmarketing Experience

The following adverse reactions have been identified during postapproval use of TEVIMBRA. Because these reactions are reported voluntarily from a population of uncertain size, it is not always possible to reliably estimate their frequency or establish a causal relationship to drug exposure.

Skin and subcutaneous tissue disorders: Stevens-Johnson syndrome, toxic epidermal necrolysis (including fatal cases).

Immune system disorders: Immune-mediated cystitis.

8 USE IN SPECIFIC POPULATIONS

8.1 Pregnancy

Risk Summary

Based on its mechanism of action, TEVIMBRA can cause fetal harm when administered to a pregnant woman [see Clinical Pharmacology (12.1)]. There are no available data on the use of TEVIMBRA in pregnant women. Animal studies have demonstrated that inhibition of the PD-1/PD-L1 pathway can lead to increased risk of immune-mediated rejection of the developing fetus resulting in fetal death (see Data). Human IgG4 immunoglobulins (IgG4) are known to cross the placental barrier; therefore, tislelizumab-jsgr has the potential to be transmitted from the mother to the developing fetus. Advise pregnant women of the potential risk to a fetus.

In the U.S. general population, the estimated background risk of major birth defects and miscarriage in clinically recognized pregnancies is 2% to 4% and 15% to 20%, respectively.

Data

Animal Data

Animal reproduction studies have not been conducted with TEVIMBRA to evaluate its effect on reproduction and fetal development. A central function of the PD-1/PD-L1 pathway is to preserve pregnancy by maintaining maternal immune tolerance to the fetus. In murine models of pregnancy, blockade of PD-L1 signaling has been shown to disrupt tolerance to the fetus and to result in an increase in fetal loss; therefore, potential risks of administering TEVIMBRA during pregnancy include increased rates of abortion or stillbirth. As reported in the literature, there were no malformations related to the blockade of PD-1 signaling in the offspring of these animals; however, immune-mediated disorders occurred in PD-1 and PD-L1 knockout mice. Based on its mechanism of action, fetal exposure to tislelizumab-jsgr may increase the risk of developing immune-mediated disorders or altering the normal immune response.

8.2 Lactation

Risk Summary

There is no information regarding the presence of tislelizumab-jsgr in human milk, or its effects on the breastfed child or on milk production. Because of the potential for serious adverse reactions in breastfed children, advise women not to breastfeed during treatment and for 4 months after the last dose of TEVIMBRA.

8.3 Females and Males of Reproductive Potential

TEVIMBRA can cause fetal harm when administered to a pregnant woman [see Use in Specific Populations (8.1)].

Pregnancy Testing

Verify pregnancy status in females of reproductive potential prior to initiating TEVIMBRA [see Use in Specific Populations (8.1)].

Contraception

Females

Advise females of reproductive potential to use effective contraception during treatment with TEVIMBRA and for 4 months after the last dose of TEVIMBRA.

8.4 Pediatric Use

The safety and effectiveness of TEVIMBRA have not been established in pediatric patients.

8.5 Geriatric Use

TEVIMBRA as a Single Agent

Of the 255 patients who were treated with TEVIMBRA for previously treated unresectable or metastatic ESCC in the clinical study RATIONALE-302, 98 (38%) were 65 years and older and 13 (5%) were 75 years and older. No overall differences in safety or effectiveness were observed between elderly patients and younger patients.

TEVIMBRA in Combination with Chemotherapy

Of the 324 patients who were treated with TEVIMBRA and platinum-containing chemotherapy as first-line treatment for unresectable advanced or metastatic ESCC in the clinical study RATIONALE-306, 149 (46%) were 65 years and older and 13 (4%) were 75 years and older. No overall differences in safety or effectiveness were observed between elderly patients and younger patients.

Of the 498 patients who were treated with TEVIMBRA in combination with platinum-containing chemotherapy for G/GEJ adenocarcinoma in the clinical study RATIONALE-305, 161 (32%) were 65 years and older, and 28 (6%) were 75 years and older. No overall differences in safety or effectiveness were observed between elderly patients and younger patients.

11 DESCRIPTION

Tislelizumab-jsgr is a programmed death receptor-1 (PD-1)–blocking antibody. Tislelizumab-jsgr is an Fc-engineered humanized monoclonal IgG4 kappa antibody with an approximate molecular weight of 147 kDa. Tislelizumab-jsgr is produced in recombinant Chinese hamster ovary (CHO) cells.

TEVIMBRA (tislelizumab-jsgr) injection is a sterile, preservative-free, clear to slightly opalescent, colorless to slightly yellow solution for intravenous use, supplied in single-dose vials. Each vial contains 100 mg of tislelizumab-jsgr monoclonal antibody in 10 mL of solution, with a concentration of 10 mg/mL, and is formulated in: citric acid monohydrate (4.2 mg), histidine (17.2 mg), L-histidine hydrochloride monohydrate (8.2 mg), polysorbate 20 (2 mg), sodium citrate (59.3 mg), trehalose (650.4 mg), and Water for Injection, USP. The pH is 6.5.

12 CLINICAL PHARMACOLOGY

12.1 Mechanism of Action

Binding of the PD-1 ligands PD-L1 and PD-L2, to the PD-1 receptor found on T cells, inhibits T-cell proliferation and cytokine production. Upregulation of PD-1 ligands occurs in some tumors and signaling through this pathway can contribute to inhibition of active T-cell immune surveillance of tumors.

Tislelizumab-jsgr binds to PD-1 and blocks its interaction with PD-L1 and PD-L2, releasing PD-1 pathway-mediated inhibition of the immune response, including the anti-tumor immune response. Tislelizumab-jsgr decreased tumor growth in xenograft models and a human PD-1 transgenic mouse model.

12.2 Pharmacodynamics

The tislelizumab-jsgr exposure-response relationship for efficacy and safety and time course of pharmacodynamic response has not been fully characterized.

12.3 Pharmacokinetics

Pharmacokinetic parameters are presented as geometric mean (% CV) unless otherwise specified.

The peak concentration (Cmax) and area under the plasma concentration versus time curve (AUC) of tislelizumab-jsgr increased dose proportionally in the dose range of 0.5 (0.2 times the approved recommended dosage in a 70 kg patient) to 10 mg/kg (3.5 times the approved recommended dosage in a 70 kg patient).

The steady-state AUCtau of tislelizumab-jsgr is 1,283 mcg/mL∙day (28.7%) and the Cmax is 110 mcg/mL (22.2%) following the approved recommended dosage. Steady-state concentration of tislelizumab-jsgr is reached after 12 weeks of repeated dosing with an every 3-week regimen and the systemic accumulation was 2.14-fold.

Distribution

The tislelizumab-jsgr steady-state total volume of distribution is 6.42 L (32.6%).

Elimination

The tislelizumab-jsgr total clearance is 0.153 L/day (29.5%) and the terminal half-life (t½) is 24 days (31%).

Specific Populations

No clinically significant differences in the pharmacokinetics of tislelizumab-jsgr were observed based on age (range: 18 to 90 years), weight (range: 32 to 130 kg), race (White, Asian, or Black), mild to moderate renal impairment (CLcr ≥30 mL/min, estimated by Cockcroft-Gault), mild to moderate hepatic impairment (total bilirubin ≤3 times ULN and any AST, estimated by NCI criteria). The effect of severe hepatic impairment (total bilirubin >3 times ULN and any AST), severe renal impairment (CLcr 15-29 mL/min), or end-stage renal disease (CLcr <15 mL/min) on the pharmacokinetics of tislelizumab-jsgr is unknown.

12.6 Immunogenicity

The observed incidence of anti-drug antibodies is highly dependent on the sensitivity and specificity of the assay. Differences in assay methods preclude meaningful comparisons of the incidence of anti-drug antibodies in the studies described below with the incidence of anti-drug antibodies in other studies, including those of tislelizumab-jsgr products.

In patients who received tislelizumab-jsgr in RATIONALE-306 for up to 26 months, the incidence of anti-tislelizumab antibodies was 22% (66/300). Among the anti-tislelizumab antibody-positive patients, the incidence of neutralizing antibodies was 1.5% (1/66).

In patients who received tislelizumab-jsgr in RATIONALE-302 for up to 22 months, the incidence of anti-tislelizumab antibodies was 14.5% (32/221). Among the anti-tislelizumab antibody-positive patients, the incidence of neutralizing antibodies was 3.1% (1/32).

In patients who received tislelizumab-jsgr in RATIONALE-305 throughout the treatment period and in the ADA analysis set, the incidence of anti-tislelizumab antibodies was 22.7% (108/475). Among the anti-tislelizumab antibody-positive patients, the incidence of neutralizing antibodies was 5.6% (6/108).

There was no significant effect of anti-drug antibodies on the pharmacokinetics of tislelizumab-jsgr. The effect of anti-drug antibodies on pharmacodynamics, safety, or effectiveness of tislelizumab-jsgr has not been fully characterized.

13 NONCLINICAL TOXICOLOGY

13.1 Carcinogenesis, Mutagenesis, Impairment of Fertility

No studies have been performed to assess the potential of tislelizumab-jsgr for carcinogenicity or genotoxicity.

In a 3-month repeat-dose toxicology study in cynomolgus monkeys, there were no notable effects in the male and female reproductive organs; however, most animals in the study were not sexually mature.

13.2 Animal Toxicology and/or Pharmacology

In animal models, inhibition of PD-L1/PD-1 signaling resulted in an increased severity of some infections and enhanced inflammatory responses. Mycobacterium tuberculosis–infected PD-1 knockout mice exhibit markedly decreased survival compared with wild-type controls, which correlated with increased bacterial proliferation and inflammatory responses in these animals. PD-1 blockade using a primate anti–PD-1 antibody was also shown to exacerbate M. tuberculosis infection in rhesus macaques. PD-L1 and PD-1 knockout mice have also shown decreased survival following infection with lymphocytic choriomeningitis virus.

14 CLINICAL STUDIES

14.1 Esophageal Squamous Cell Carcinoma

First-line Treatment of Unresectable or Metastatic Esophageal Carcinoma (ESCC) in Patients Whose Tumors Express PD-L1 (≥1)

The efficacy of TEVIMBRA, in combination with chemotherapy, was evaluated in RATIONALE-306 (NCT03783442), a global, randomized, placebo-controlled, double-blind study in patients with unresectable, recurrent, or metastatic esophageal squamous cell carcinoma (ESCC).

Patients were enrolled regardless of their PD-L1 expression level. PD-L1 expression was evaluated at a central laboratory using the Ventana PD-L1 (SP263) assay that identified PD-L1 staining on both tumor and tumor-associated immune cells (Tumor Area Positivity or TAP). A retrospective scoring of tumor PD-L1 status using Combined Positive Score (CPS) was also conducted using the PD-L1–stained tumor specimens used for randomization.

Patients should not have received prior systemic therapy for advanced or metastatic disease. A treatment-free interval of at least 6 months was required if there was prior neoadjuvant/adjuvant therapy with platinum-based chemotherapy. The trial excluded patients who had active leptomeningeal disease or uncontrolled brain metastasis, active autoimmune disease, a medical condition requiring systemic corticosteroids or immunosuppressants, or evidence of fistula or complete esophageal obstruction not amenable to treatment.

Patients were randomized (1:1) to receive either TEVIMBRA 200 mg every 3 weeks or placebo in combination with investigator's choice of chemotherapy (ICC) on a 21-day cycle. Patients received TEVIMBRA until disease progression assessed by the investigator per RECIST v1.1, or until unacceptable toxicity. The chemotherapy doublet regimen consists of:

- Platinum (cisplatin [60 to 80 mg/m^2 IV, on Day 1] or oxaliplatin [130 mg/m^2 IV, on Day 1]) and a fluoropyrimidine (fluorouracil [750 to 800 mg/m^2 IV, on Days 1 to 5] or capecitabine [1000 mg/m^2 orally twice daily, on Days 1 to 14])

or

- Platinum (cisplatin [60 to 80 mg/m^2 IV, on Day 1 or 2] or oxaliplatin [130 mg/m^2 IV, on Day 1 or 2]) and (paclitaxel 175 mg/m^2 IV, on Day 1)

Cross-over between treatment arms or between fluoropyrimidine and paclitaxel during the study treatment period was not allowed.

Patient randomization was stratified by geographic region (Asia [excluding Japan] versus Japan versus Rest of World), prior definitive therapy (yes versus no), and investigator choice of chemotherapy (ICC; platinum with fluoropyrimidine versus platinum with paclitaxel).

Tumor assessments were performed every 6 weeks for the first 48 weeks, then every 9 weeks thereafter.

The primary efficacy outcome measure was overall survival (OS) in the Intent-to-Treat (ITT) population. Secondary outcome measures included progression-free survival (PFS), objective response rate (ORR), and duration of response (DoR) as assessed by the investigator per RECIST v1.1. Additional analyses of efficacy outcome measures were also conducted based on PD-L1 TAP ≥1% and CPS ≥1.

A total of 649 patients were randomized. The trial population characteristics were median age 64 years (range: 26 to 84 years), 48% were ≥65 years of age, 87% were male, 75% were Asian, and 24% were White. Eighty-six percent had metastatic disease and 14% had locally advanced disease; 99.8% of patients had histological confirmation of squamous cell carcinoma. Baseline ECOG performance status was 0 (33%) or 1 (67%). Thirty-four percent of patients had tumors that expressed PD-L1 TAP ≥10%, 74% had PD-L1 TAP ≥1%, and 74% had PD-L1 CPS ≥1. Fifty-five percent of patients received platinum (cisplatin or oxaliplatin) and paclitaxel-containing regimens, and 45% received platinum (cisplatin or oxaliplatin) and fluoropyrimidine-containing regimens.

RATIONALE-306 demonstrated a statistically significant improvement in OS for patients randomized to TEVIMBRA in combination with chemotherapy compared to placebo in combination with chemotherapy. Exploratory analysis of OS in the population with TAP <1% population and in the CPS <1 population showed hazard ratios of 1.34 (95% CI 0.73, 2.46) and 1.52 (95% CI 0.81, 2.84), respectively, indicating that the improvement in the ITT population was primarily attributed to the results observed in the subgroup of patients with PD-L1 ≥1.

Efficacy results are shown in Table 9, Figure 1, and Figure 2.

Table 9: Efficacy results in RATIONALE-306
Endpoint | TEVIMBRA + Chemotherapy (N=231) | Placebo + Chemotherapy (N=250) | TEVIMBRA + Chemotherapy (N=233) | Placebo + Chemotherapy (N=247)
Endpoint | PD-L1 TAP ≥1% |  | PD-L1 CPS ≥1
Overall Survival (OS)
Deaths n (%) | 141 (61) | 177 (70.8) | 141 (61) | 175 (71)
Median (months) [Medians were estimated by Kaplan-Meier method with 95% CIs estimated using the method of Brookmeyer and Crowley.] (95% CI) | 16.8 (15.3, 20.8) | 9.6 (8.9, 11.8) | 16.8 (15.3, 20.8) | 9.6 (8.9, 11.8)
HR [Estimated by Cox proportional hazards model.] (95% CI) | 0.66 (0.53, 0.82) |  | 0.65 (0.52,0.81)
Progression-Free Survival (PFS)
Events, n (%) | 152 (66) | 199 (80) | 153 (66) | 195 (79)
Median (months) (95% CI) | 7.2 (6.8, 8.5) | 5.5 (4.5, 5.8) | 7.1 (6.8, 8.3) | 5.5 (4.5, 5.8)
HR (95% CI) | 0.56 (0.45, 0.70) |  | 0.57 (0.46, 0.71)
Objective Response Rate (ORR) [Confirmed responses.]
Responders, n | 134 | 90 | 134 | 89
ORR, % | 58 | 36 | 58 | 36
95% CI [Exact Clopper-Person-2-sided CI.] | (51, 65) | (30, 42) | (51, 64) | (30, 42)
Complete response (CR), n (%) | 11 (4.8) | 5 (2) | 11 (4.7) | 5 (2)
Partial response, n (%) | 123 (53) | 85 (34) | 123 (53) | 84 (34)
Duration of Response (DoR)
Median DoR (months) (95% CI) | 7.2 (6.2, 9.6) | 5.7 (4.4, 7.3) | 7.6 (6.6, 9.7) | 5.6 (4.4, 7.3)
CI = confidence interval; HR = hazard ratio.

Figure 1: Kaplan-Meier Curve for Overall Survival in RATIONALE-306 (PD-L1 TAP ≥1%)

Figure 2: Kaplan-Meier Curve for Overall Survival in RATIONALE-306 (PD-L1 CPS ≥1)

Efficacy results from the exploratory retrospective analysis with CPS scoring were generally consistent with the efficacy results for TAP subgroups detailed in Table 9 and Figure 1.

Previously Treated Unresectable or Metastatic Esophageal Squamous Cell Carcinoma (ESCC)

RATIONALE-302 (NCT03430843) was a multicenter, randomized (1:1), open-label trial in 512 adult patients with unresectable advanced or metastatic ESCC who progressed on or after prior systemic chemotherapy.

Patients were enrolled regardless of their tumor PD-L1 expression level. PD-L1 expression was evaluated at a central laboratory using the Ventana PD-L1 (SP263) assay that identified PD-L1 staining on both tumor and tumor-associated immune cells (TAP). The trial excluded patients who received a prior immune checkpoint inhibitor, had brain or leptomeningeal metastases that were symptomatic or required treatment, active autoimmune disease, a medical condition requiring systemic corticosteroids or immunosuppressants, or apparent tumor invasion of organs adjacent to the esophageal tumor.

Patients were randomized (1:1) to receive either TEVIMBRA 200 mg every 3 weeks or investigator's choice of chemotherapy (ICC), all given intravenously: paclitaxel 135-175 mg/m^2 every 3 weeks or 80 to 100 mg/m^2 weekly, docetaxel 75 mg/m^2 every 3 weeks, or irinotecan 125 mg/m^2 on Days 1 and 8 of every 3-week cycle. Patients were treated until disease progression assessed by the investigator or unacceptable toxicity.

Randomization was stratified by geographic region (Asia [excluding Japan] vs Japan vs US/EU), ECOG performance status (0 vs 1), and ICC option. Tumor assessments were conducted every 6 weeks for the first 6 months, then every 9 weeks until disease progression.

The major efficacy outcome measure was overall survival (OS) in the Intent-to-Treat (ITT) population. Additional efficacy outcome measures were investigator-assessed progression-free survival (PFS), overall response rate (ORR), and duration of response (DOR) per RECIST v1.1.

A total of 512 patients were enrolled and randomized to TEVIMBRA (n=256) or ICC (n=256) (irinotecan [46%], paclitaxel [33%], or docetaxel [21%]). Of the 512 patients, 142 (28%) had PD-L1 ≥10%, 222 (43%) had PD-L1 <10%, and 148 (29%) had unknown baseline PD-L1 status.

The trial population characteristics were: median age of 62 years (range: 35 to 86), 38% age ≥65; 84% male; 19% White and 80% Asian; 95% had metastatic disease. All patients had received at least one prior anti-cancer systemic therapy. Baseline ECOG performance status was 0 (25%) or 1 (75%).

RATIONALE-302 demonstrated a statistically significant improvement in OS for patients randomized to TEVIMBRA as compared with ICC. OS results by PD-L1 CPS level (<1 and ≥1) were not studied.

Efficacy results are shown in Table 10 and Figure 3.

Table 10: Efficacy Results in RATIONALE-302 in ITT Population
Endpoint | TEVIMBRA (N=256) | ICC (N=256)
Overall Survival
Deaths n (%) | 197 (77) | 213 (83.2)
Median (months) [Estimated using Kaplan-Meier method.] (95% CI) | 8.6 (7.5, 10.4) | 6.3 (5.3, 7)
Hazard ratio [Based on Cox regression model stratified by baseline ECOG status and ICC option.] (95% CI) | 0.7 (0.57, 0.85)
p-value [One-sided p-value based on log-rank test stratified by ECOG performance status and ICC option.] | 0.0001
Progression-Free Survival
Disease progression or death (%) | 223 (87.1) | 180 (70.3)
Median (months) (95% CI) | 1.6 (1.4, 2.7) | 2.1 (1.5, 2.7)
Hazard ratio (95% CI) | 0.83 (0.67, 1.01)
Objective Response Rate [Confirmed response.]
ORR (%) (95% CI) | 15.2 (11.1, 20.2) | 6.6 (3.9, 10.4)
Complete response n (%) | 5 (2) | 1 (0.4)
Partial response n (%) | 34 (13.3) | 16 (6.3)
Duration of Response
Median (months) (95% CI) | 10.3 (6.5, 13.2) | 6.3 (2.8, 8.5)
CI = confidence interval, ORR = objective response rate.

Figure 3: Kaplan-Meier Curve for Overall Survival in RATIONALE-302 (ITT)

14.2 Gastric Cancer

Previously Untreated, Unresectable, or Metastatic HER2-Negative Gastric or Gastroesophageal Junction (G/GEJ) Adenocarcinoma in Patients Whose Tumors Express PD-L1 (≥1)

RATIONALE-305 (NCT03777657) was a randomized, multicenter, placebo-controlled, double-blind trial in patients with HER2-negative previously untreated unresectable or metastatic G/GEJ adenocarcinoma.

Patients were enrolled regardless of their tumor PD-L1 expression level, which was evaluated prospectively at a central laboratory using the VENTANA PD-L1 (SP263) assay that identified PD-L1 staining on both tumor and tumor-associated immune cells (TAP). A retrospective scoring of tumor PD-L1 status using Combined Positive Score (CPS) was also conducted using the PD-L1-stained tumor specimens used for randomization.

The trial excluded patients who had active leptomeningeal disease or uncontrolled brain metastasis, and patients with active autoimmune disease or history of autoimmune diseases, or a medical condition requiring systemic corticosteroids or immunosuppressants.

Patients were randomized to receive either TEVIMBRA 200 mg every 3 weeks or placebo in combination with investigator's choice of chemotherapy on a 21-day cycle. TEVIMBRA (or placebo) was administered until disease progression or unacceptable toxicity.

The chemotherapy doublets regimen consisted of:

- CAPOX: Oxaliplatin 130 mg/m^2 IV on Day 1 for up to 6 cycles and capecitabine 1000 mg/m^2 orally twice daily for 14 consecutive days. Capecitabine treatment could be continued beyond 6 cycles

or

- FP: Cisplatin 80 mg/m^2 IV, Day 1, and 5-FU 800 mg/m^2/day IV continuous infusion over 24 hours daily Day 1-5. Cisplatin and 5-FU were given for up to 6 cycles

Cross-over between treatment arms was not allowed.

Patient randomization was stratified by geographic region (China [including Taiwan], vs Japan and South Korea vs rest of the world, including US and Europe); PD-L1 expression (PD-L1 TAP score ≥5% vs PD-L1 TAP score <5%); presence of peritoneal metastasis (yes vs no); and ICC option (oxaliplatin plus capecitabine vs cisplatin plus 5-FU).

Tumor assessments were performed every 6 weeks for the first 48 weeks and thereafter approximately every 9 weeks.

The primary efficacy outcome measures were OS in the PD-L1 TAP score ≥5% population and in the Intent-to-Treat (ITT) population. Secondary outcome measures included progression-free survival (PFS), objective response rate (ORR), and duration of response (DoR) as assessed by the investigator per RECIST v1.1. Additional analyses of efficacy outcome measures were also conducted based on PD-L1 TAP ≥1% and CPS ≥1.

A total of 997 patients were randomized. The trial population characteristics were median age 61 years (range: 23 to 86 years), 35% ≥65 years of age, 69% male; 75% Asian, 22% White, and 0% Black or African American. Eighty percent had primary stomach tumor; 89% had PD-L1 TAP ≥1% and 86% had PD-L1 CPS ≥1, and 99% of patients had metastatic disease at baseline. Baseline ECOG performance status was 0 (32%) or 1 (68%). Ninety-three percent of patients received CAPOX and 7% received FP.

RATIONALE-305 demonstrated a statistically significant improvement in OS for patients randomized to TEVIMBRA in combination with chemotherapy compared with placebo plus chemotherapy in the PD-L1 TAP ≥5% population and in the ITT population. Exploratory analyses of OS in the TAP <1% population and in the CPS <1 population showed hazard ratios of 0.98 (95% CI: 0.64, 1.50) and 1.01 (95% CI: 0.66, 1.52) respectively, indicating that the improvement in the ITT population was primarily attributed to the results observed in the subgroup of patients with PD-L1 ≥1.

Efficacy results are summarized in Table 11, Figure 4, and Figure 5.

Table 11: Efficacy Results in RATIONALE-305
Endpoint | TEVIMBRA + Chemotherapy (N=432) | Placebo + Chemotherapy (N=453) | TEVIMBRA + Chemotherapy (N=420) | Placebo + Chemotherapy (N=434)
Endpoint | PD-L1 TAP ≥1% |  | PD-L1 CPS ≥1
Overall Survival
Deaths n (%) | 318 (74) | 370 (82) | 308 (73) | 356 (82)
Median (months) [Medians were estimated by Kaplan-Meier method with 95% CIs estimated using the method of Brookmeyer and Crowley.] (95% CI) | 15.0 (13.3, 16.7) | 12.8 (12.1, 14.1) | 15.1 (13.6, 17.2) | 12.9 (12.1, 14.1)
HR [Estimated by Cox proportional hazards model.] (95% CI) | 0.78 (0.67, 0.90) |  | 0.78 (0.67, 0.91)
Progression-Free Survival
Events, n (%) | 316 (73) | 364 (80) | 303 (72) | 348 (80)
Median [Based on confirmed response.] (months) (95% CI) | 6.9 (5.7, 7.2) | 5.9 (5.6, 6.9) | 7.0 (5.7, 7.7) | 6.4 (5.6, 6.9)
HR (95% CI) | 0.78 (0.67, 0.91) |  | 0.77 (0.66, 0.90)
Objective Response Rate
ORR, n | 206 | 186 | 204 | 183
ORR, % | 48 | 41 | 49 | 42
95% CI (%) [Exact Clopper-Pearson 2-sided confidence interval.] | (43, 53) | (37, 46) | (44, 53) | (37, 47)
Complete response, n (%) | 15 (3.5) | 15 (3.3) | 16 (3.8) | 16 (3.7)
Partial response, n (%) | 191 (44) | 171 (38) | 188 (45) | 167 (38)
Duration of Response
Median (months) (95% CI) | 8.6 (7.8, 10.4) | 7.2 (5.8, 8.3) | 8.6 (7.8, 10.4) | 7.2 (5.8, 8.5)
Abbreviations: CI = confidence interval, HR = hazard ratio, ORR = objective response rate.

Figure 4: Kaplan-Meier Curve for Overall Survival in RATIONALE-305 (PD-L1 TAP ≥1%)

Figure 5: Kaplan-Meier Curve for Overall Survival in RATIONALE-305 (PD-L1 CPS ≥1)

An exploratory subgroup analysis of OS in 40 patients with MSI-H tumors irrespective of PD-L1 status showed a HR of 0.66 (0.3, 1.43).

16 HOW SUPPLIED/STORAGE AND HANDLING

How Supplied

TEVIMBRA injection is a clear to slightly opalescent, colorless to slightly yellow solution supplied in a carton containing one 100 mg/10 mL (10 mg/mL) single-dose vial (NDC 72579-121-01).

Storage

Store in a refrigerator at 2°C to 8°C (36°F to 46°F) in the original carton to protect from light.

Do not freeze. Do not shake.

17 PATIENT COUNSELING INFORMATION

Advise patients to read the FDA-approved patient labeling (Medication Guide).

Immune-Mediated Adverse Reactions

Inform patients of the risk of immune-mediated adverse reactions that may be severe or fatal, may occur after discontinuation of treatment, and may require corticosteroid treatment and interruption or discontinuation of TEVIMBRA. These reactions may include:

- Pneumonitis: Advise patients to contact their healthcare provider immediately for new or worsening cough, chest pain, or shortness of breath [see Warnings and Precautions (5.1)].
- Colitis: Advise patients to contact their healthcare provider immediately for diarrhea, or severe abdominal pain [see Warnings and Precautions (5.1)].
- Hepatitis: Advise patients to contact their healthcare provider immediately for jaundice, severe nausea or vomiting, pain on the right side of the abdomen, or easy bruising or bleeding [see Warnings and Precautions (5.1)].
- Endocrinopathies: Advise patients to contact their healthcare provider immediately for signs or symptoms of hypophysitis, adrenal insufficiency, hypothyroidism, hyperthyroidism, thyroiditis, or Type 1 diabetes mellitus [see Warnings and Precautions (5.1)].
- Nephritis: Advise patients to contact their healthcare provider immediately for signs or symptoms of nephritis [see Warnings and Precautions (5.1)].
- Dermatologic Adverse Reactions: Advise patients to contact their healthcare provider immediately for any signs or symptoms of severe skin reactions, SJS, TEN, or DRESS [see Warnings and Precautions (5.1)].
- Other Immune-Mediated Adverse Reactions:
  - Advise patients that immune-mediated adverse reactions can occur and may involve any organ system, and to contact their healthcare provider immediately for any new or worsening signs or symptoms [see Warnings and Precautions (5.1)].
  - Advise patients of the risk of solid organ transplant rejection and other transplant (including corneal graft) rejection and to contact their healthcare provider immediately for signs or symptoms of organ transplant rejection [see Warnings and Precautions (5.1)].

Infusion-Related Reactions

Advise patients to contact their healthcare provider immediately for signs or symptoms of infusion-related reactions [see Warnings and Precautions (5.2)].

Complications of Allogeneic Hematopoietic Stem Cell Transplantation Complications

Advise patients of potential risk of post-allogeneic hematopoietic stem cell transplantation complications (HSCT) [see Warnings and Precautions (5.3)].

Embryo-Fetal Toxicity

Advise females of reproductive potential of the potential risk to a fetus and to inform their healthcare provider of a known or suspected pregnancy [see Warnings and Precautions (5.4), Use in Specific Populations (8.1, 8.3)].

Advise females of reproductive potential to use effective contraception during treatment with TEVIMBRA and for 4 months after the last dose [see Warnings and Precautions (5.4), Use in Specific Populations (8.1, 8.3)].

Lactation

Advise women not to breastfeed during treatment with TEVIMBRA and for 4 months after the last dose [see Use in Specific Populations (8.2)].

Manufactured by:
BeOne Medicines USA, Inc.
Pennington, NJ 08534
U.S. License No. 2400

TEVIMBRA® is a registered trademark owned by BeOne Medicines I GmbH or its affiliates.
© BeOne Medicines I GmbH, 2025. All Rights Reserved.

Medication Guide
TEVIMBRA® (teh-vim-brah)
(tislelizumab-jsgr)
injection

What is the most important information I should know about TEVIMBRA?
TEVIMBRA is a medicine that may treat certain cancers by working with your immune system. TEVIMBRA can cause your immune system to attack normal organs and tissues in any area of your body and can affect the way they work. These problems can sometimes become severe or life-threatening and can lead to death. You can have more than one of these problems at the same time. These problems may happen anytime during treatment or even after your treatment has ended.
Call or see your healthcare provider right away if you develop any new or worsening symptoms, including:
Lung problems

- new or worsening cough

- shortness of breath

- chest pain

Intestinal problems

- diarrhea (loose stools) or more bowel movements than usual
- stools that are black, tarry, sticky, or have blood or mucus
- severe stomach-area (abdomen) pain or tenderness

Liver problems

- yellowing of your skin or the whites of your eyes
- severe nausea or vomiting
- pain on the right side of your stomach area (abdomen)

- dark urine (tea colored)
- bleeding or bruising more easily than normal

Hormone gland problems

- headaches that will not go away or unusual headaches
- eye sensitivity to light
- eye problems
- rapid heartbeat
- increased sweating
- extreme tiredness
- weight gain or weight loss
- feeling more hungry or thirsty than usual

- urinating more often than usual
- hair loss
- feeling cold
- constipation
- your voice gets deeper
- dizziness or fainting
- changes in mood or behavior, such as decreased sex drive, irritability, or forgetfulness

Kidney problems

- decrease in your amount of urine
- blood in your urine

- swelling in your ankles
- loss of appetite

Skin problems

- rash
- itching
- skin blistering or peeling

- painful sores or ulcers in your mouth or in your nose, throat, or genital area
- fever or flu-like symptoms
- swollen lymph nodes

Problems can also happen in other organs and tissues. These are not all of the signs and symptoms of immune system problems that can happen with TEVIMBRA. Call or see your healthcare provider right away for new or worsening symptoms, which may include:

- chest pain, irregular heartbeat, shortness of breath, swelling of ankles
- confusion, sleepiness, memory problems, changes in mood or behavior, stiff neck, balance problems, tingling or numbness of the arms or legs
- double vision, blurry vision, sensitivity to light, eye pain, changes in eyesight
- persistent or severe muscle pain or weakness, muscle cramps
- low red blood cells, bruising

Infusion reactions that can sometimes be severe or life-threatening. Signs or symptoms of infusion reactions may include:

- chills or shaking
- itching or rash
- flushing
- shortness of breath or wheezing

- dizziness
- feeling like passing out
- fever
- back or neck pain

Rejection of a transplanted organ or tissue. Your healthcare provider should tell you what signs and symptoms you should report and monitor you, depending on the type of organ or tissue transplant that you have had.
Complications, including graft-versus-host-disease (GVHD), in people who have received a bone marrow (stem cell) transplant that uses donor stem cells (allogeneic). These complications can be serious and can lead to death. These complications may happen if you underwent transplantation either before or after being treated with TEVIMBRA. Your healthcare provider will monitor you for these complications.
Getting medical treatment right away may help keep these problems from becoming more serious.
Your healthcare provider will check you for these problems during your treatment with TEVIMBRA. Your healthcare provider may treat you with corticosteroid or hormone replacement medicines. Your healthcare provider may also need to delay or completely stop treatment with TEVIMBRA if you have severe side effects.

What is TEVIMBRA?
TEVIMBRA is a prescription medicine used to treat adults with:

- cancer of the tube that connects your throat to your stomach (esophageal cancer).
  - TEVIMBRA may be used in combination with chemotherapy that contains platinum as your first treatment when your esophageal cancer:
    - is a type called squamous cell carcinoma, and
    - cannot be removed with surgery or has spread to other parts of the body (metastatic), and
    - your tumor tests positive for "PD-L1."
  - TEVIMBRA may be used alone when your esophageal cancer:
    - is a type called squamous cell carcinoma, and
    - cannot be removed with surgery or has spread to other parts of the body (metastatic), and
    - you have had previous treatment that did not include a PD-(L)1 inhibitor medicine.
- cancer of the stomach (gastric cancer) or cancer where the esophagus joins the stomach (gastroesophageal junction cancer).
  - TEVIMBRA may be used in combination with chemotherapy that contains platinum and fluoropyrimidine as your first treatment when your gastric or gastroesophageal junction cancer:
    - cannot be removed with surgery or has spread to other parts of the body (metastatic), and
    - your tumor tests positive for "PD-L1."

It is not known if TEVIMBRA is safe and effective in children.

Before receiving TEVIMBRA, tell your healthcare provider about all of your medical conditions, including if you:

- have immune system problems such as Crohn's disease, ulcerative colitis, or lupus
- have received an organ or tissue transplant, including corneal transplant
- have received or plan to receive a stem cell transplant that uses donor stem cells (allogeneic)
- have received radiation treatment to your chest area
- have a condition that affects your nervous system, such as myasthenia gravis or Guillain-Barré syndrome
- are pregnant or plan to become pregnant. TEVIMBRA can harm your unborn baby.
  Females who are able to become pregnant:
  - Your healthcare provider will do a pregnancy test before you start treatment with TEVIMBRA.
  - You should use an effective method of birth control during your treatment and for 4 months after your last dose of TEVIMBRA. Talk to your healthcare provider about birth control methods that you can use during this time.
  - Tell your healthcare provider right away if you become pregnant or think you may be pregnant during treatment with TEVIMBRA.
- are breastfeeding or plan to breastfeed. It is not known if TEVIMBRA passes into your breast milk. Do not breastfeed during treatment with TEVIMBRA and for 4 months after your last dose of TEVIMBRA.

Tell your healthcare provider about all the medicines you take, including prescription and over-the-counter medicines, vitamins, and herbal supplements.

How will I receive TEVIMBRA?

- Your healthcare provider will give you TEVIMBRA into your vein through an intravenous (IV) line over 30 to 120 minutes depending on the dose you are receiving.
- TEVIMBRA is usually given every 2, 3, 4, or 6 weeks depending on the dose you are receiving.
- Your healthcare provider will decide how many treatments you need.
- Your healthcare provider will do blood tests to check you for certain side effects.
- If you miss any appointment, call your healthcare provider as soon as possible to reschedule your appointment.

What are the possible side effects of TEVIMBRA?
TEVIMBRA may cause serious side effects. See "What is the most important information I should know about TEVIMBRA?"
The most common side effects of TEVIMBRA when used in combination with platinum-containing chemotherapy include:

- decreased white blood cell count
- decreased salt (sodium) in your blood
- increased glucose in your blood
- decreased red blood cell count (anemia)

- tiredness
- decreased appetite
- increase in certain liver blood tests
- decreased potassium in your blood

- increase in certain kidney blood tests
- decreased calcium in your blood
- diarrhea
- mouth sores
- vomiting

The most common side effects of TEVIMBRA when used alone include:

- increased blood sugar
- decreased red blood cell (anemia) and white blood cell counts
- decreased salt (sodium) in your blood

- decreased albumin in the blood
- increase in certain liver blood tests
- tiredness

- muscle and bone pain
- decreased weight
- cough

The most common side effects of TEVIMBRA in combination with platinum and fluoropyrimidine-based chemotherapy include:

- nausea
- tiredness
- decreased appetite
- decreased red blood cell count (anemia)
- numbness, pain, tingling, or burning in your hands or feet

- vomiting
- decreased platelet count
- decreased white blood cell count
- increase in certain liver blood tests

- diarrhea
- stomach-area (abdominal) pain
- decreased weight
- fever

These are not all the possible side effects of TEVIMBRA.
Call your doctor for medical advice about side effects. You may report side effects to FDA at 1-800-FDA-1088.

General information about the safe and effective use of TEVIMBRA.
Medicines are sometimes prescribed for purposes other than those listed in a Medication Guide. You can ask your healthcare provider or pharmacist for more information about TEVIMBRA that is written for health professionals.

What are the ingredients in TEVIMBRA?
Active ingredient: tislelizumab-jsgr
Inactive ingredients: citric acid monohydrate, histidine, L-histidine hydrochloride monohydrate, polysorbate 20, sodium citrate, trehalose, and Water for Injection.
Manufactured by: BeOne Medicines USA, Inc. Pennington, NJ 08534
U.S. License No. 2400
TEVIMBRA® is a registered trademark owned by BeOne Medicines I GmbH or its affiliates.
© BeOne Medicines I GmbH, 2025. All Rights Reserved.
For more information, call 1-833-969-2463 or go to www.TEVIMBRA.com

This Medication Guide has been approved by the U.S. Food and Drug Administration.

Revised: 12/2025

PRINCIPAL DISPLAY PANEL - 10 mL Vial Carton

NDC 72579-121-01
Rx only

TEVIMBRA®
tislelizumab-jsgr
injection

100 mg/10 mL
(10 mg/mL)

For Intravenous Infusion
After Dilution

Dispense with Medication Guide

One 10 mL single-dose vial
Discard unused portion